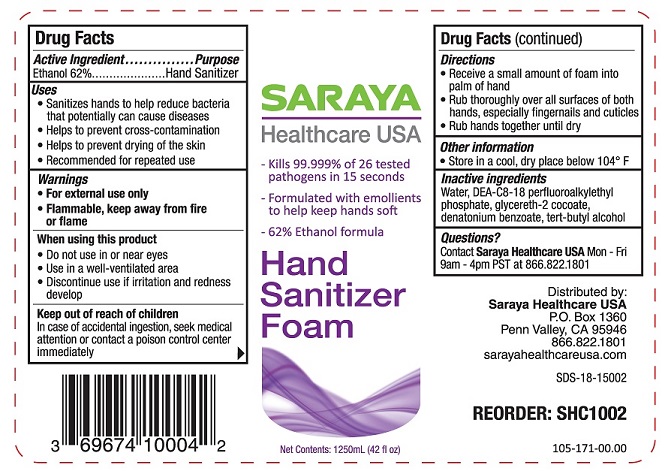 DRUG LABEL: Hand Sanitizer
NDC: 69674-100 | Form: LIQUID
Manufacturer: Saraya Healthcare
Category: otc | Type: HUMAN OTC DRUG LABEL
Date: 20260113

ACTIVE INGREDIENTS: ALCOHOL 62 mL/100 mL
INACTIVE INGREDIENTS: DIETHANOLAMINE BIS(C8-C18 PERFLUOROALKYLETHYL)PHOSPHATE; TERT-BUTYL ALCOHOL; WATER; GLYCERETH-2 COCOATE; DENATONIUM BENZOATE

SARAYA HAND SANITIZER FOAM 69674-100

Active Ingredient

Ethanol 62%

Purpose

Hand Sanitizer

Uses

- Sanitizes hands to help reduce bacteria that potentially can cause diseases
- Helps to prevent cross-contamination
- Helps to prevent drying of the skin
- Recommended for repeated use

Warnings

- For external use only
- Flammable, keep away from fire or flame

When using this product

- Do not use in or near eyes
- Use in a well-ventilated area
- Discontinue use if irritation and redness develop

Keep out of reach of children

In case of accidental ingestion, seek medical attention or contact a poison control center immediately

Directions

- Receive a small amount of foam into palm of hand
- Rub thoroughly over all surfaces of both hands, especially fingernails and cuticles
- Rub hands together until dry

Other information

- Store in a cool, dry place below 104°F

Inactive ingredients

Water, DEA-C8-18 perfluoroalkylethyl phosphate, glycereth-2 cocoate, denatonium benzoate, tert-butyl alcohol

Questions?

Contact Saraya Healthcare USAMon - Fri

9am - 4pm PST at 866.822.1801

Distributed by:

Saraya Healthcare USA

P.O. Box 1360

Penn Valley, CA 95946

866.822.1801

sarayahealthcareusa.com

SARAYAHealthcare USA

- Kills 99.999% of 26 tested pathogens in 15 seconds

- Formulated with emollients to help keep hands soft

- 62% Ethanol formula

Hand Sanitizer Foam

Net Contents: 1250mL (42 fl oz)